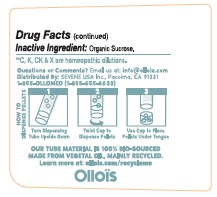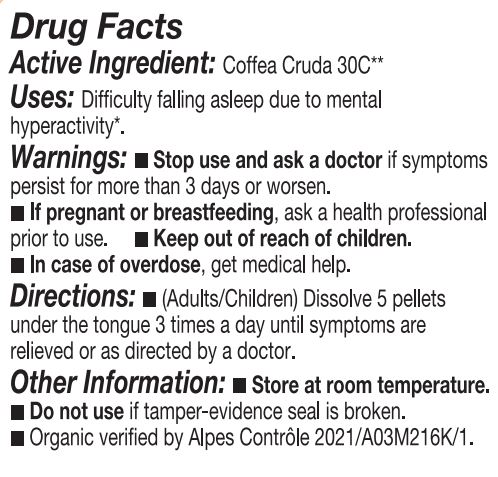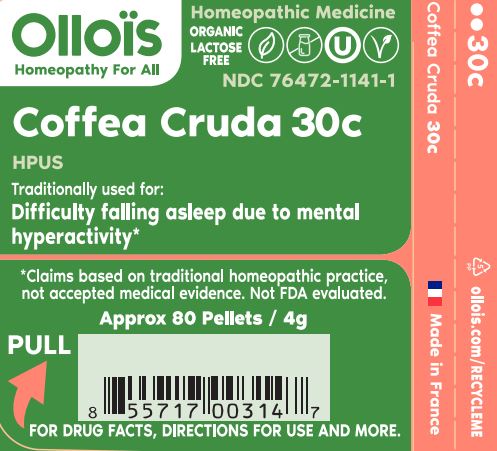 DRUG LABEL: Coffea Cruda 30c
NDC: 76472-1141 | Form: PELLET
Manufacturer: SEVENE USA
Category: homeopathic | Type: HUMAN OTC DRUG LABEL
Date: 20240124

ACTIVE INGREDIENTS: ARABICA COFFEE BEAN 30 [hp_C]/1 1
INACTIVE INGREDIENTS: SUCROSE

Sevene USA (as PLD) - COFFEA CRUDA 30c (76472-1141)

ACTIVE INGREDIENT:

Homeopathic dilution of HPUS Coffea Cruda 30c.

TRADITIONALLY USED FOR:

Difficulty falling asleep due to mental hyperactivity*

DIRECTIONS:

(adults/children) Dissolve 5 pellets under the tongue 3 times a day until symptoms are relieved or as directed by a physician.

USE:

Condition listed above or as directed by a physician.

WARNINGS:

Stop use and ask a physician if symptoms persist for more than 3 days or worsen.

PREGNANCY OR BREAST FEEDING

If pregnant or breast-feeding, ask a health professional before use.

Keep out of reach of children.

OTHER INFORMATION:

Store at room temperature.

Do not use if pellet-dispenser seal is broken.

INACTIVE INGREDIENT:

Sucrose.

QUESTIONS?

info@ollois.com * www.ollois.com * Made in France. Not reviewed by FDA and not guaranteed to be effective. This Homeopathic dilution may not be suseptible to scientific measurement.